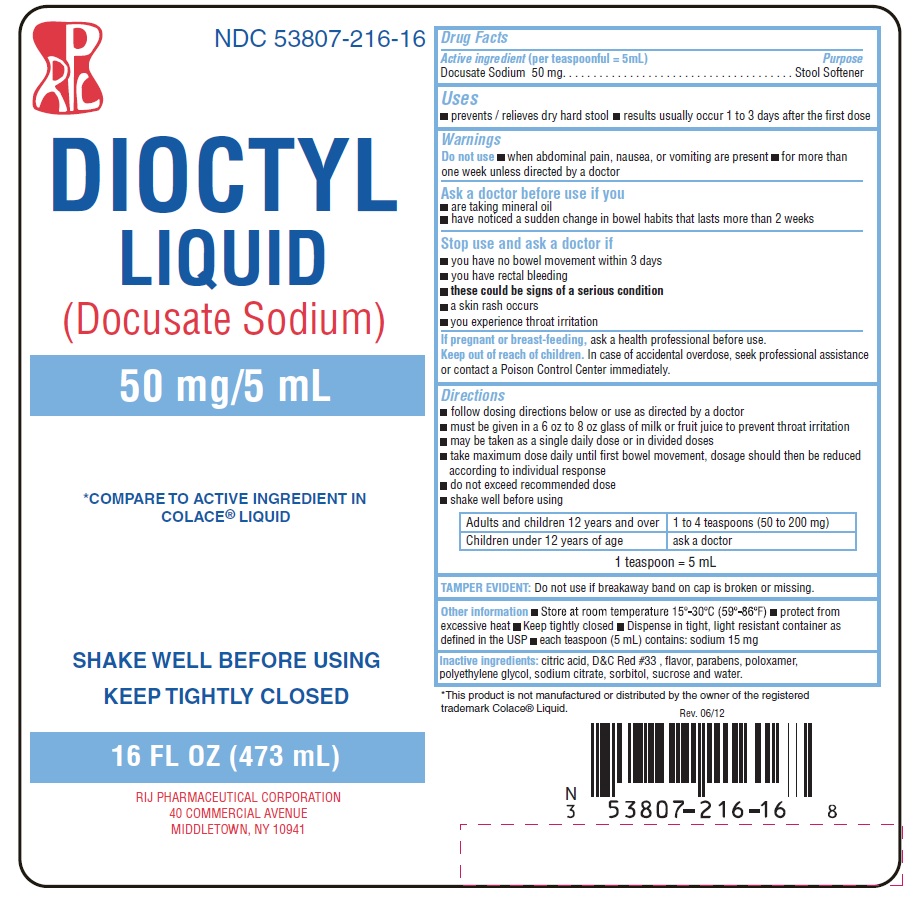 DRUG LABEL: Docusate Sodium Liquid
NDC: 53807-216 | Form: LIQUID
Manufacturer: Rij Pharmaceutical Corporation
Category: otc | Type: HUMAN OTC DRUG LABEL
Date: 20180430

ACTIVE INGREDIENTS: Docusate sodium 10 mg/1 mL
INACTIVE INGREDIENTS: anhydrous citric acid; D&C red no. 33; methylparaben; propylparaben; propylene glycol; sodium citrate; water; Poloxamer 407; SUCROSE; SORBITOL

Drug Facts

Active Ingredient (per teaspoonful = 5 mL)

Docusate Sodium 50 mg

Purpose

Stool Softener

Uses

- prevents / relieves dry hard stool
- results usually occur 1 to 3 days after the first dose

Warnings

Do not use

- when abdominal pain, nausea, or vomiting are present
- for more than one week unless directed by a doctor

Ask a doctor before use if you

- are taking mineral oil
- have noticed a sudden change in bowel habits that lasts more than 2 weeks

Stop use and ask a doctor if

- you have no bowel movement within 3 days
- you have rectal bleeding
- these could be signs of a serious condition
- a skin rash occurs
- you experience throat irritation

PREGNANCY OR BREAST FEEDING

If pregnant or breast feeding, ask a health professional before use.

Keep out of reach of children. In case of accidental overdose, seek professional assisstance or contact a Poison Control Center immediately.

Directions

- follow dosing directions below or take as directed by doctor
- must be given in a 6 to 8 oz glass of milk or fruit juice to prevent throat irritation
- may be taken as a single daily dose or in divided doses
- take maximum dose daily until first bowel movement, dosage should then be reduced according to individual response
- do not exceed recommended dose
- shake well before using

Adults and children 12 years and over | 1 to 4 teaspoons (50 to 200 mg)
Children under 12 years of age | ask a doctor

1 teaspoon = 5 mL

TAMPER EVIDENT: Do not use if breakaway band on cap is broken or missing.

Other information

- Store at room temperature 15°-30°C (59°-86°F)
- protect from excessive heat
- Keep tightly closed
- Dispense in tight, light resistant container as defined in the USP
- each teaspoon (5 mL) contains: sodium 15 mg

Inactive ingredients

citric acid, D&C Red #33, flavor, parabens, poloxamer, propylene glycol, sodium citrate, sorbitol, sucrose, and water.